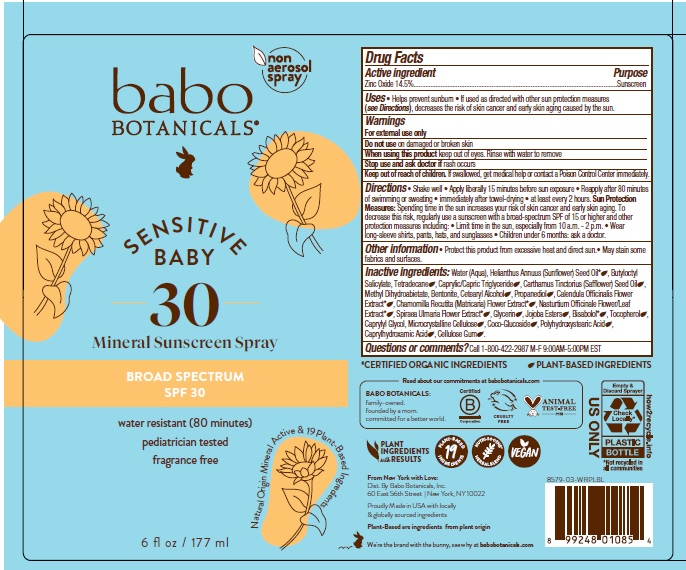 DRUG LABEL: Babo Botanicals Sensitive Baby Mineral Sunscreen SPF30
NDC: 79265-9758 | Form: SPRAY
Manufacturer: Babo Botanicals, Inc.
Category: otc | Type: HUMAN OTC DRUG LABEL
Date: 20231026

ACTIVE INGREDIENTS: ZINC OXIDE 145 mg/1 mL
INACTIVE INGREDIENTS: TETRADECANE; WATER; BENTONITE; CAPRYLYL GLYCOL; LEVOMENOL; CETOSTEARYL ALCOHOL; CHAMOMILE; GLYCERIN; SUNFLOWER OIL; HYDROGENATED JOJOBA OIL, RANDOMIZED; METHYL DIHYDROABIETATE; PROPANEDIOL; CARBOXYMETHYLCELLULOSE SODIUM, UNSPECIFIED FORM; BUTYLOCTYL SALICYLATE; CALENDULA OFFICINALIS FLOWER; CAPRYLHYDROXAMIC ACID; MEDIUM-CHAIN TRIGLYCERIDES; SAFFLOWER OIL; COCO GLUCOSIDE; MICROCRYSTALLINE CELLULOSE; NASTURTIUM OFFICINALE FLOWERING TOP; POLYHYDROXYSTEARIC ACID (2300 MW); FILIPENDULA ULMARIA FLOWER; TOCOPHEROL

Babo Botanicals Sensitive Baby Mineral Sunscreen SPF30

Active ingredient

Zinc Oxide 14.5%

Purpose

Sunscreen

Uses

- Helps prevent sunburn
- If used as directed with other sun protection measures (see Directions), decreases the risk of skin cancer and early skin aging caused by the sun.

Warnings

For external use only.

Do not use

on damaged or broken skin.

When using this product

keep out of eyes. Rinse with water to remove.

Stop use and ask doctor

if rash occurs

Keep out of reach of children.

If swallowed, get medical help or contact a Poison Control Center immediately.

Directions

- Shake well
- Apply liberally 15 minutes before sun exposure.
- Reapply after 80 minutes of swimming or sweating
- immediately after towel-drying
- at least every 2 hours.

Sun Protection Measures. Spending time in the sun increases your risk of skin cancer and early skin aging. To decrease this risk, regularly use a sunscreen with a broad-spectrum SPF of 15 or higher and other protection measures including

- Limit time in the sun, especially from 10 a.m. – 2 p.m.
- Wear long-sleeve shirts, pants, hats, and sunglasses.
- Children under 6 months; ask a doctor.

Other information

- Protect this product from excessive heat and direct sun.
- May stain some fabrics and surfaces.

Inactive Ingredients

Water (Aqua), Helianthus Annuus (Sunflower) Seed Oil*, Butyloctyl Salicylate, Tetradecane, Caprylic/Capric Triglyceride, Carthamus Tinctorius (Safflower) Seed Oil, Methyl Dihydroabietate, Bentonite, Cetearyl Alcohol, Propanediol, Calendula Officinalis Flower Extract*, Chamomilla Recutita (Matricaria) Flower Extract*, Nasturtium Officinale Flower/Leaf Extract*, Spiraea Ulmaria Flower Extract*, Glycerin, Jojoba Esters, Bisabolol*, Tocopherol, Caprylyl Glycol, Microcrystalline Cellulose, Coco-Glucoside, Polyhydroxystearic Acid, Caprylhydroxamic Acid, Cellulose Gum.

*Certified Organic Ingredients

Questions or comments?

Call 1-800-422-2987 M-F 9:00AM-5:00PM EST